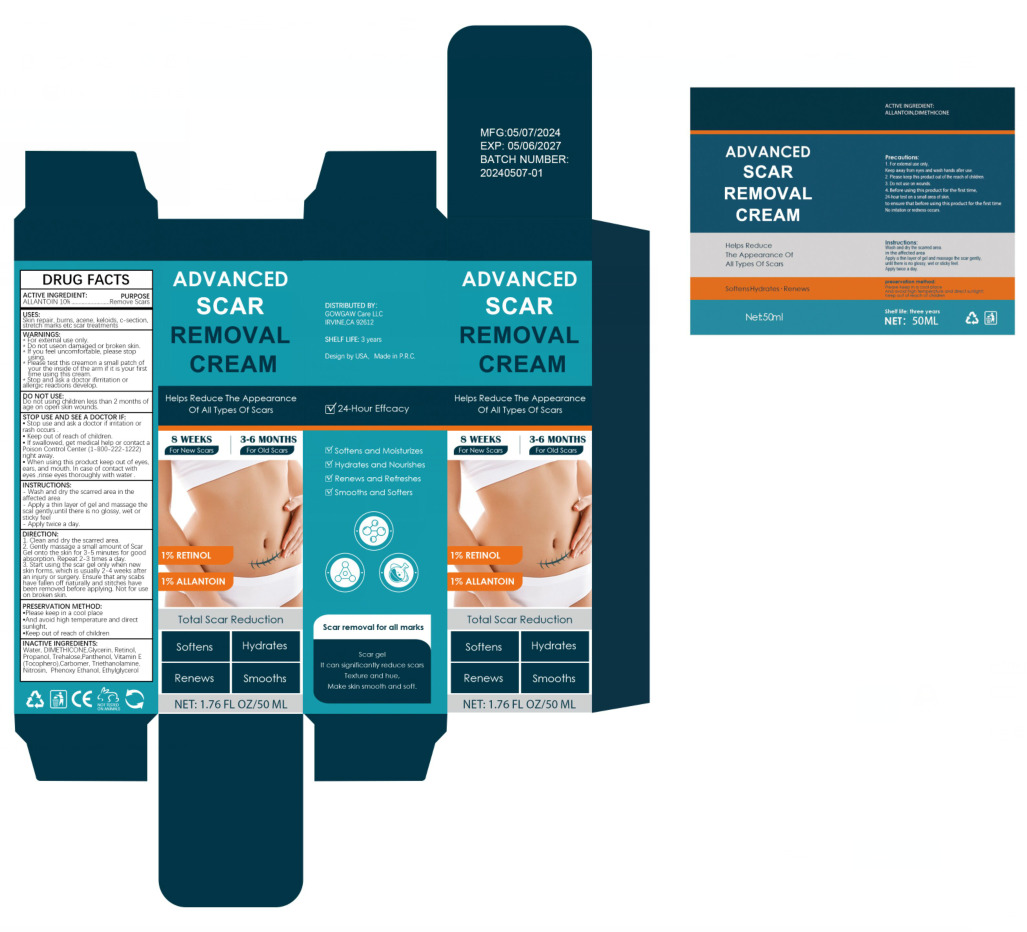 DRUG LABEL: Scar Removal Cream
NDC: 84322-003 | Form: CREAM
Manufacturer: Shenzhen Gaoye E-commerce Co., Ltd
Category: otc | Type: HUMAN OTC DRUG LABEL
Date: 20240629

ACTIVE INGREDIENTS: ALLANTOIN 10 g/100 mL
INACTIVE INGREDIENTS: TROLAMINE; CARBOXYPOLYMETHYLENE; TREHALOSE; WATER; DIMETHICONE; GLYCERIN; RETINOL; PROPYL ALCOHOL; PANTHENOL

84322-003

Active Ingredient(s)

ALLANTOIN 10%

Purpose

Remove Scars

Use

Skin repair, burns, acene, keloids, c-section, stretch marks etc scar treatments

Warnings

* For external use only.

* Do not useon damaged or broken skin.

* If you feel uncomfortable, please stop using.

* Please test this creamon a small patch of your the inside of the arm if it is your first time using this cream.

* Stop and ask a doctor ifirritation or allergic reactions develop.

Do not use

Do not using children less than 2 months of age on open skin wounds.

When using this product keep out of eyes, ears, and mouth. In case of contact with eyes, rinse eyes thoroughly with water.

• Stop use and ask a doctor if irritation or rash occurs .

• Keep out of reach of children.

• If swallowed, get medical help or contact a Poison Control Center (1-800-222-1222) right away.

• When using this product keep out of eyes, ears, and mouth. In case of contact with eyes ,rinse eyes thoroughly with water .

Keep out of reach of children. If swallowed, get medical help or contact a Poison Control Center right away.

Directions

1. Clean and dry the scarred area.

2. Gently massage a small amount of Scar Gel onto the skin for 3-5 minutes for good absorption. Repeat 2-3 times a day.

3. Start using the scar gel only when new skin forms, which is usually 2-4 weeks after an injury or surgery. Ensure that any scabs have fallen off naturally and stitches have been removed before applying. Not for use on broken skin.

Other information

•Please keep in a cool place

•And avoid high temperature and direct sunlight,

•Keep out of reach of children

Inactive ingredients

Water, DIMETHICONE, Glycerin, Retinol, Propanol, Trehalose, Panthenol, Vitamin E (Tocophero),

Carbomer, Triethanolamine, Nitrosin, Phenoxy Ethanol, Ethylglycerol